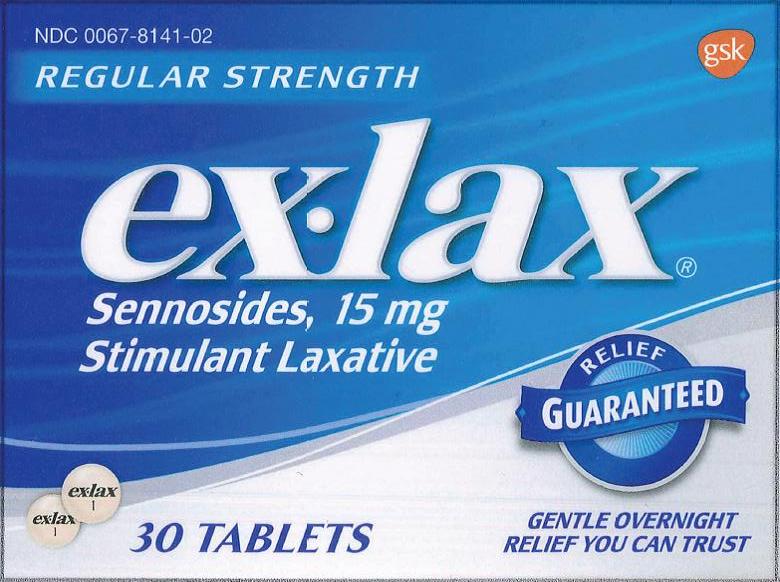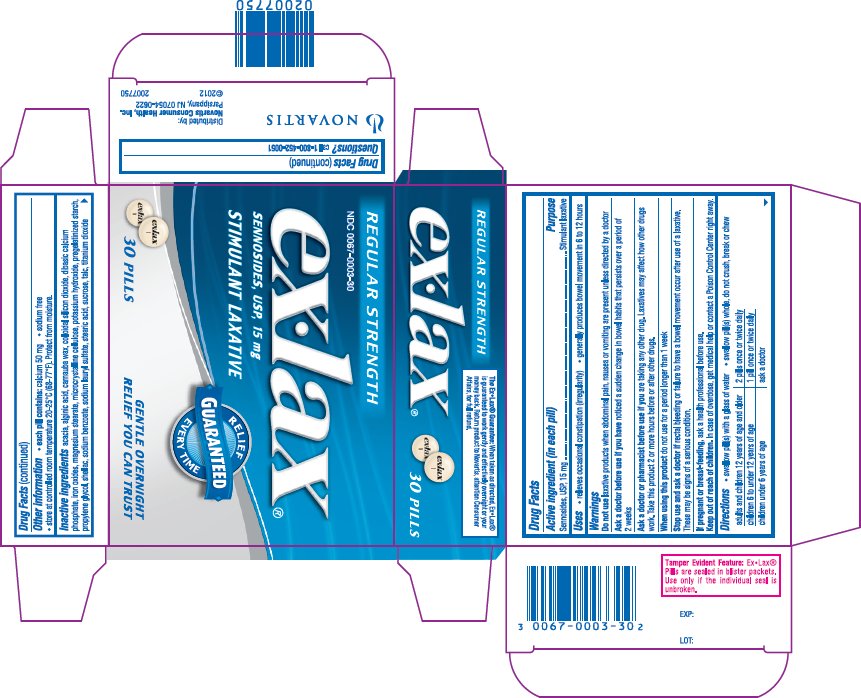 DRUG LABEL: EX-LAX
NDC: 0067-0003 | Form: PILL
Manufacturer: Haleon US Holdings LLC
Category: otc | Type: HUMAN OTC DRUG LABEL
Date: 20240313

ACTIVE INGREDIENTS: SENNOSIDES 15 mg/1 1
INACTIVE INGREDIENTS: ACACIA; ALGINIC ACID; CARNAUBA WAX; SILICON DIOXIDE; ANHYDROUS DIBASIC CALCIUM PHOSPHATE; FERROSOFERRIC OXIDE; FERRIC OXIDE RED; FERRIC OXIDE YELLOW; MAGNESIUM STEARATE; MICROCRYSTALLINE CELLULOSE; POTASSIUM HYDROXIDE; PROPYLENE GLYCOL; SHELLAC; SODIUM BENZOATE; SODIUM LAURYL SULFATE; STEARIC ACID; SUCROSE; TALC; TITANIUM DIOXIDE

Drug Facts

Active ingredient (in each tablet)

Sennosides 15 mg

Purpose

Stimulant laxative

Uses

- relieves occasional constipation (irregularity)
- generally produces bowel movement in 6 to 12 hours

Warnings

Do not use

laxative products when abdominal pain, nausea, or vomiting are present unless directed by a doctor

Ask a doctor before use if you have

noticed a sudden change in bowel habits that persists over a period of 2 weeks

Ask a doctor or pharmacist before use if you are

taking any other drug. Laxatives may affect how other drugs work. Take this product 2 or more hours before or after other drugs.

When using this product

do not use for a period longer than 1 week

Stop use and ask a doctor if

rectal bleeding or failure to have a bowel movement occur after use of a laxative. These may be signs of a serious condition.

If pregnant or breast-feeding,

ask a health professional before use.

Keep out of reach of children.

In case of overdose, get medical help or contact a Poison Control Center right away.

Directions

- swallow tablet(s) with a glass of water
- swallow tablet(s) whole, do not crush, break or chew

adults and children 12 years of age and older | 2 tablets once or twice daily
children 6 to under 12 years of age | 1 tablet once or twice daily
children under 6 years of age | ask a doctor

Other information

- each tablet contains: calcium 45 mg, magnesium 5mg
- store at controlled room temperature 20-25°C (68-77°F)

Inactive ingredients (0067-0003)

acacia, alginic acid, carnauba wax, colloidal silicon dioxide, dibasic calcium phosphate, iron oxides, magnesium stearate, microcrystalline cellulose, potassium hydroxide, pregelatinized starch, propylene glycol, shellac, sodium benzoate, sodium lauryl sulfate, stearic acid, sucrose, talc, titanium dioxide

Inactive Ingredients (0067-8141)

acacia, calcium carbonate, carnauba wax, corn starch, dibasic calcium phosphate, iron oxide black, iron oxide red, iron oxide yellow, magnesium stearate, methylparaben, microcrystalline cellulose, polyethylene glycol, polyvinyl alcohol, povidone, propylene glycol, propylparaben, shellac, silicon dioxide, sodium benzoate, sodium lauryl sulfate, sucrose, talc, titanium dioxide

Questions ?

call 1-855-221-5432

Principal Display Panel

NDC 0067-0003-30

Regular Strength

ex•lax®

SENNOSIDES, USP, 15 mg

STIMULANT LAXATIVE

RELIEF GUARANTEED EVERY TIME

GENTLE OVERNIGHT RELIEF YOU CAN TRUST

The Ex•Lax® Guarantee: When taken as directed, Ex•Lax® is guaranteed to work gently and effectively overnight or your money back. Return product to Novartis, attention Consumer Affairs, for full refund.

Tamper Evident Feature: Ex•Lax® Pills are sealed in blister packets. Use only if the individual seal is unbroken.

Trademarks are owned by or licensed to GSK group of companies

Distributed by: Novartis Consumer Health, Inc.

Parsippany, NJ 07054-0622

Principal Display Panel

NDC 0067-8141-02

ex•lax®

SENNOSIDES, 15 mg

REGULAR STRENGTH

STIMULANT LAXATIVE

RELIEF GUARANTEED

GENTLE OVERNIGHT RELIEF YOU CAN TRUST

The Ex•Lax® Guarantee: When taken as directed, Ex•Lax® is guaranteed to work gently and effectively overnight or your money back. Return product to GSK, attention Consumer Affairs, for full refund.

Tamper Evident Feature: Ex•Lax® Tablets are sealed in blister packets. Use only if the individual seal is unbroken.

Trademarks are owned by or licensed to the GSK group of companies.

Distributed by:

GSK Consumer Healthcare

Warren, NJ 07059

©2017 GSK or its licensor. All rights reserved

13143